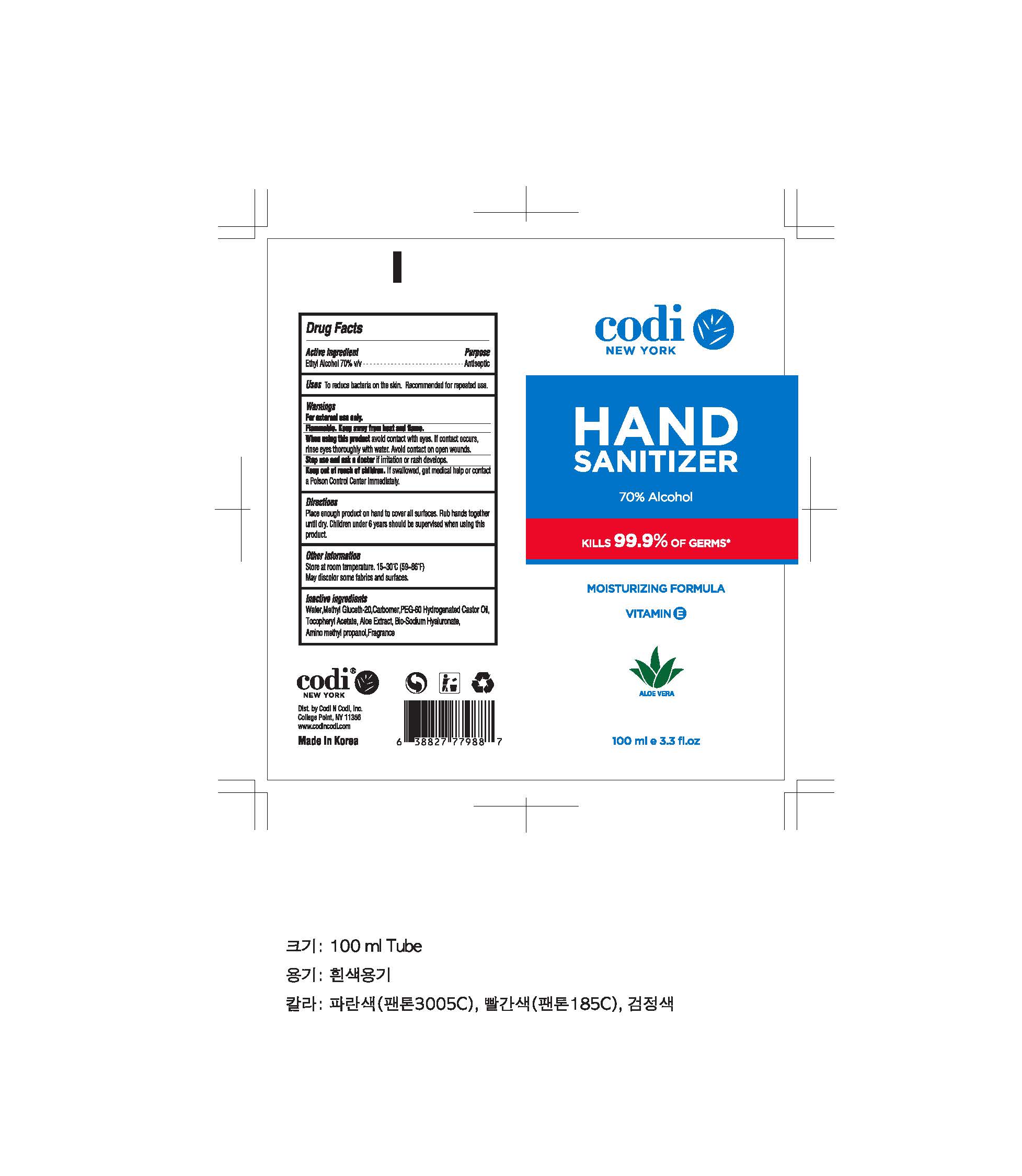 DRUG LABEL: Codi HAND SANITIZER
NDC: 78296-0002 | Form: GEL
Manufacturer: YOUSU trading
Category: otc | Type: HUMAN OTC DRUG LABEL
Date: 20200527

ACTIVE INGREDIENTS: ALCOHOL 70 mL/100 mL
INACTIVE INGREDIENTS: WATER; CARBOMER HOMOPOLYMER, UNSPECIFIED TYPE; ALOE

Drug Facts

ACTIVE INGREDIENT

Alcohol

INACTIVE INGREDIENT

Water, Methyl Gluceth-20, Carbomer, PEG-60 Hydrogenated Castor Oil, Tocopheryl Acetate, Aloe Extract, Bio-Sodium Hyaluronate, Amino methyl propanol, Fragrance

PURPOSE

Antiseptic

KEEP OUT OF REACH OF THE CHILDREN

INDICATIONS AND USAGE

For the external use only

WARNINGS

For external use only.

Flammable, keep away from fire or flame.

When using this product keep out of eyes. If contact with eyes occurs, rinse promptly and thoroughly with water.

Stop use and ask a doctor if significant irritation or sensitization develops.

Keep out of reach of children. If swallowed, get medical help or contact a Poison Control Center right away.

DOSAGE AND ADMINISTRATION

Place enough product on hand to cover all surfaces. Rub hands together until dry. Children under 6 years should be supervised when using this product.